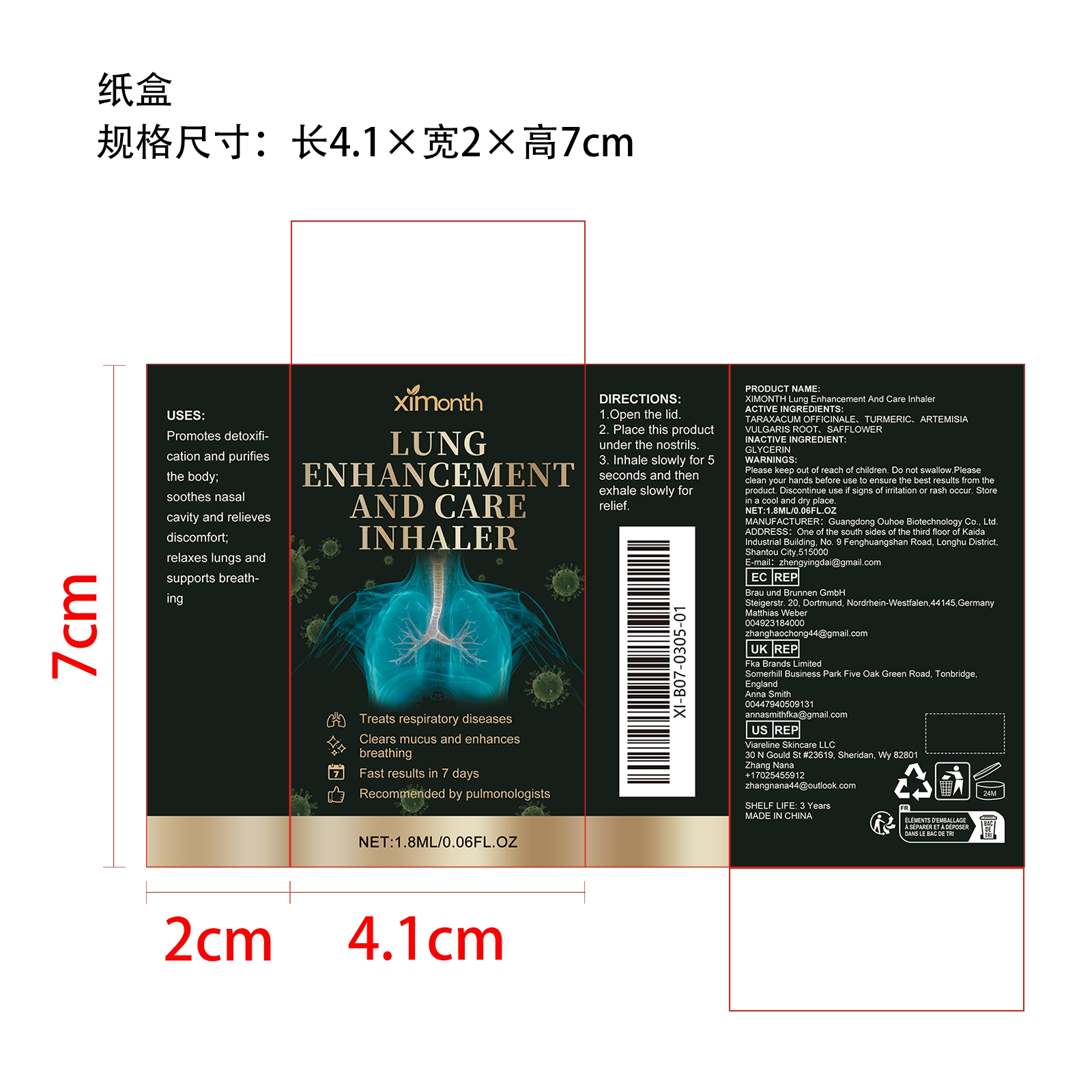 DRUG LABEL: XIMONTH Lung Enhancement And Care Inhaler
NDC: 84744-054 | Form: LIQUID
Manufacturer: Guangdong Ouhoe Biotechnology Co., Ltd.
Category: otc | Type: HUMAN OTC DRUG LABEL
Date: 20241022

ACTIVE INGREDIENTS: TURMERIC 0.18 mg/1.8 mg; TARAXACUM OFFICINALE 0.54 mg/1.8 mg; ARTEMISIA VULGARIS ROOT 0.27 mg/1.8 mg; SAFFLOWER 1.27 mg/1.8 mg
INACTIVE INGREDIENTS: GLYCERIN 0.54 mg/1.8 mg

ACTIVE INGREDIENTS

TARAXACUM OFFICINALE,TURMERIC,ARTEMISIA VULGARIS ROOT,SAFFLOWER

PURPOSE

Promotes detoxification and purifies the body; soothes nasal cavity and relieves discomfort; relaxes lungs and supports breathing

USE

1.Open the lid.

2. Place this product ndeors.

3. Inhale slowly for 5 seconds and then exhale slowly for relief.

WARNINGS

Please keep out of reach of children. Do not swallow.Please clean your hands before use to ensure the best results from the product. Discontinue use if signs of irritation or rash occur. Store in a cool and dry place.

DO NOT USE

Discontinue use if signs of irritation or rash occur.

STOP USE

Discontinue use if signs of irritation or rash occur.

KEEP OUT OF REACH OF CHILDREN

Please keep out of reach of children. Do not swallow.

STORAGE AND HANDLING

Store in a cool and dry place.

INACTIVE INGREDIENT

GLYCERIN